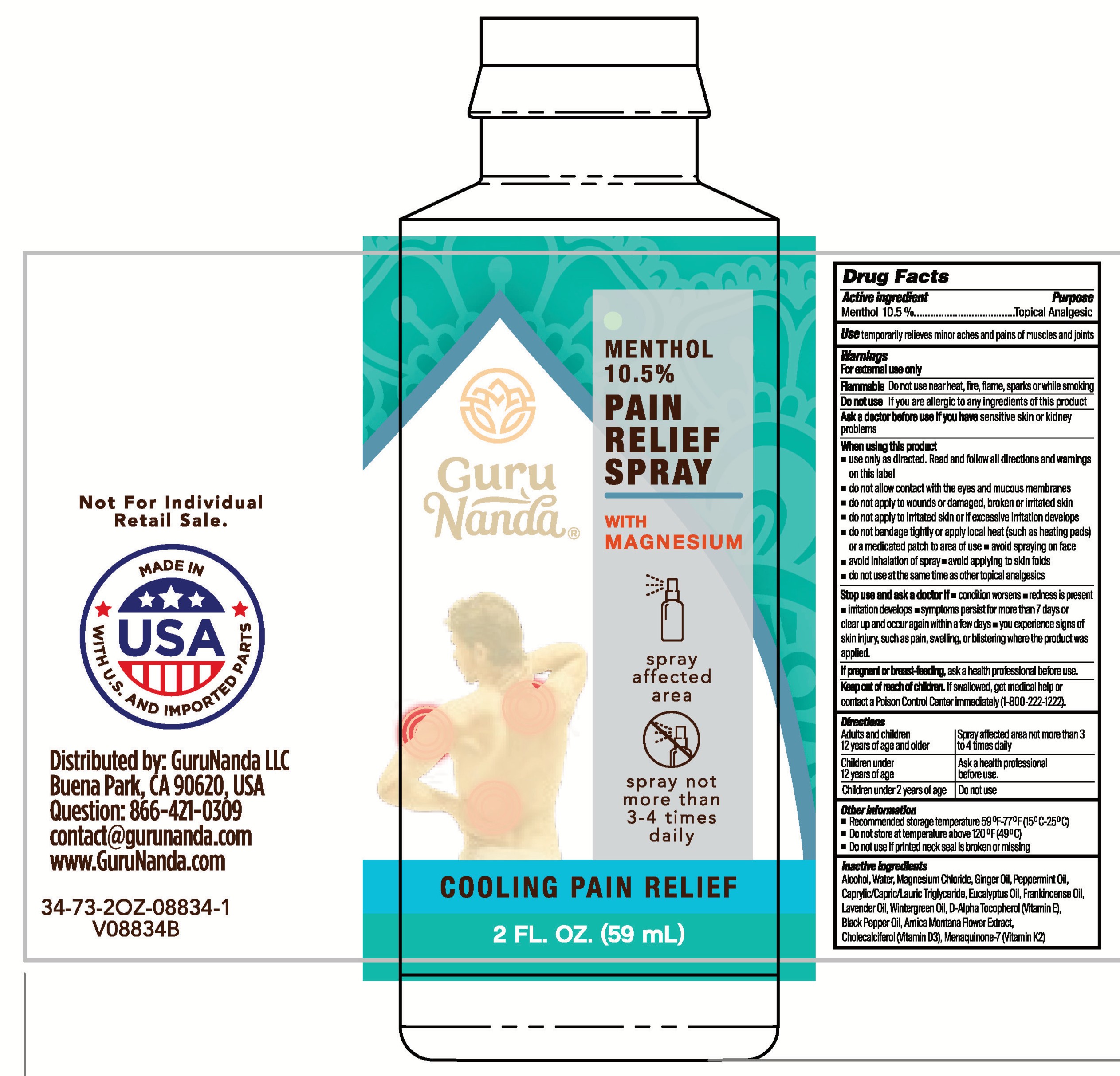 DRUG LABEL: GuruNanda Pain Relief
NDC: 70708-834 | Form: SPRAY
Manufacturer: GURUNANDA, LLC
Category: otc | Type: HUMAN OTC DRUG LABEL
Date: 20260119

ACTIVE INGREDIENTS: LEVOMENTHOL 105 mg/1 mL
INACTIVE INGREDIENTS: .ALPHA.-TOCOPHEROL, D-; ARNICA MONTANA FLOWER; EUCALYPTUS OIL; PEPPERMINT OIL; CHOLECALCIFEROL; ALCOHOL; GINGER OIL; WATER; BLACK PEPPER OIL; LAVENDER OIL; MAGNESIUM CHLORIDE; MENAQUINONE-7; CAPRYLIC/CAPRIC/LAURIC TRIGLYCERIDE; FRANKINCENSE OIL; GAULTHERIA PROCUMBENS (WINTERGREEN) LEAF OIL

GuruNanda Pain Relief Spray

Active ingredient

Menthol 10.5%

Purpose

Topical Analgesic

Use

temporariliy relieves minor aches and pains of muscles and joints

Warnings

For external use only

Flammable Do not use near heat, fire, flame, sparks or while smoking

Do not use

If you are allergic to any ingredients of this product

Ask a doctor before use if you have

sensitive skin or kidney problems

Stop use and ask a doctor if

condition worsens, redness is present, irritation develops, symptoms persist for more than 7 days or clear up and occur again within a few days, you experience signs of skin injury, such as pain, swelling, or blistering where the product was applied.

When using this product

- use only as directed. Read and follow all directions and warnings on this label
- do not allow contact with the eyes and mucous membranes
- do not apply to wounds or damaged, broken or irritated skin
- do not apply to irritated skin or if excessive irration develops
- do not bandage tightly or apply local heat (such as heating pads) or a medicated patch to area of use
- avoid spraying on face
- avoid inhalation of spray
- avoid applying to skin folds
- do not use at the same time as other topical analgesics

If pregnant or breast-feeding

ask a health professional before use.

Keep out of reach of children.

If swallowed, get medical help or contact a Poison Control Center immediately (1-800-222-1222).

Directions

Adults and children 12 years of age and older: Spray affected area not more than 3 to 4 times daily

Children under 12 years of age: Ask a health professional before use.

Children under 2 years of age: Do not use

Other information

- Recommended storage temperature 59°F-77°F (15°C-25°C)
- Do not store at temperature above 120°F (49°C)
- Do not use if printed neck seal is broken or missing

Inactive ingredients

Alcohol, Water, Magnesium Chloride, Ginger Oil, Peppermint Oil, Caprylic/Capric/Lauric Triglyceride, Eucalyptus Oil, Frankincense Oil, Lavender Oil, Wintergreen Oil, D-Alpha Tocopherol (Vitamin E), Black Pepper Oil, Arnica Montana Flower Extract, Cholecalciferol (Vitamin D3, Menaquinone-7 (Vitamin K2)